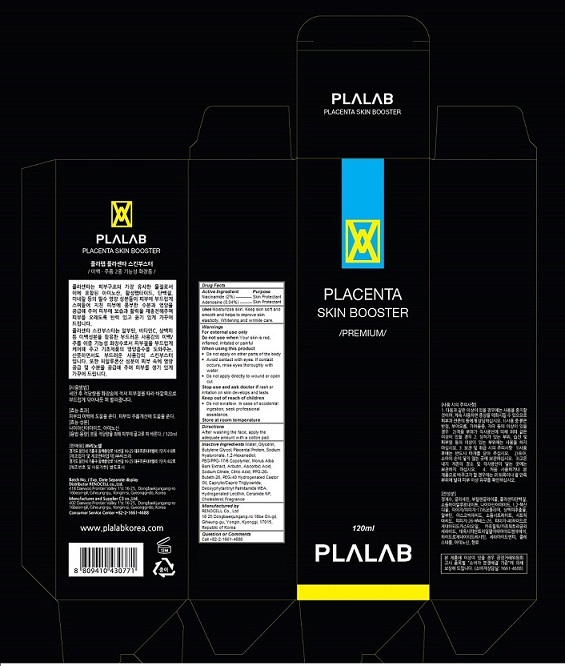 DRUG LABEL: Plalab Placenta Skin Booster
NDC: 70326-105 | Form: LIQUID
Manufacturer: RENOCELL Co., Ltd
Category: otc | Type: HUMAN OTC DRUG LABEL
Date: 20151224

ACTIVE INGREDIENTS: NIACINAMIDE 0.02 1/120 mL; ADENOSINE 0.0004 1/120 mL
INACTIVE INGREDIENTS: water; GLYCERIN; Butylene Glycol; SUS SCROFA PLACENTA; HYALURONATE SODIUM; 1,2-HEXANEDIOL; PEG/PPG-17/6 COPOLYMER; MORUS ALBA BARK; ARBUTIN; Ascorbic Acid; DISODIUM HYDROGEN CITRATE; CITRIC ACID MONOHYDRATE; PPG-26-Buteth-26; POLYOXYL 40 HYDROGENATED CASTOR OIL; MEDIUM-CHAIN TRIGLYCERIDES; DEOXYPHYTANTRIYL (2-HYDROXYETHYL)PALMITAMIDE; HYDROGENATED SOYBEAN LECITHIN; CERAMIDE NP; CHOLESTEROL

Plalab Placenta Skin Booster